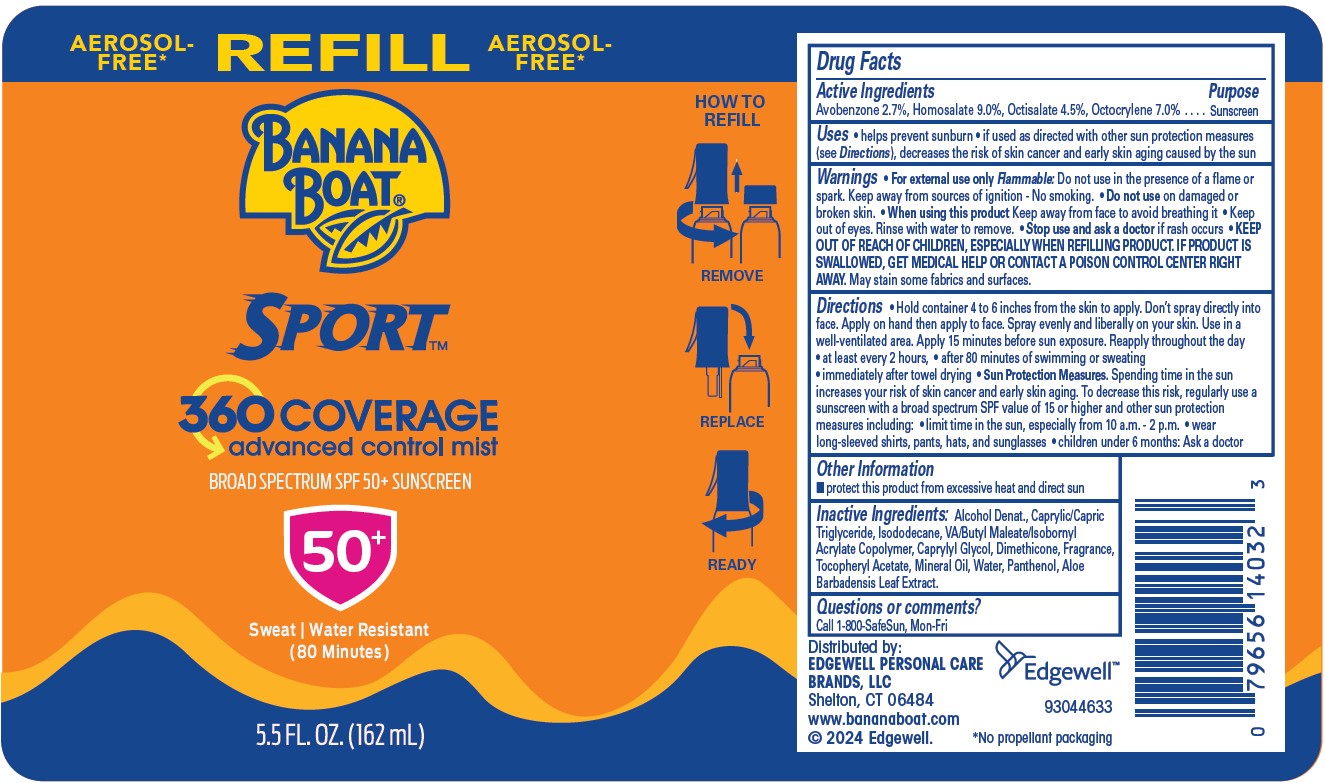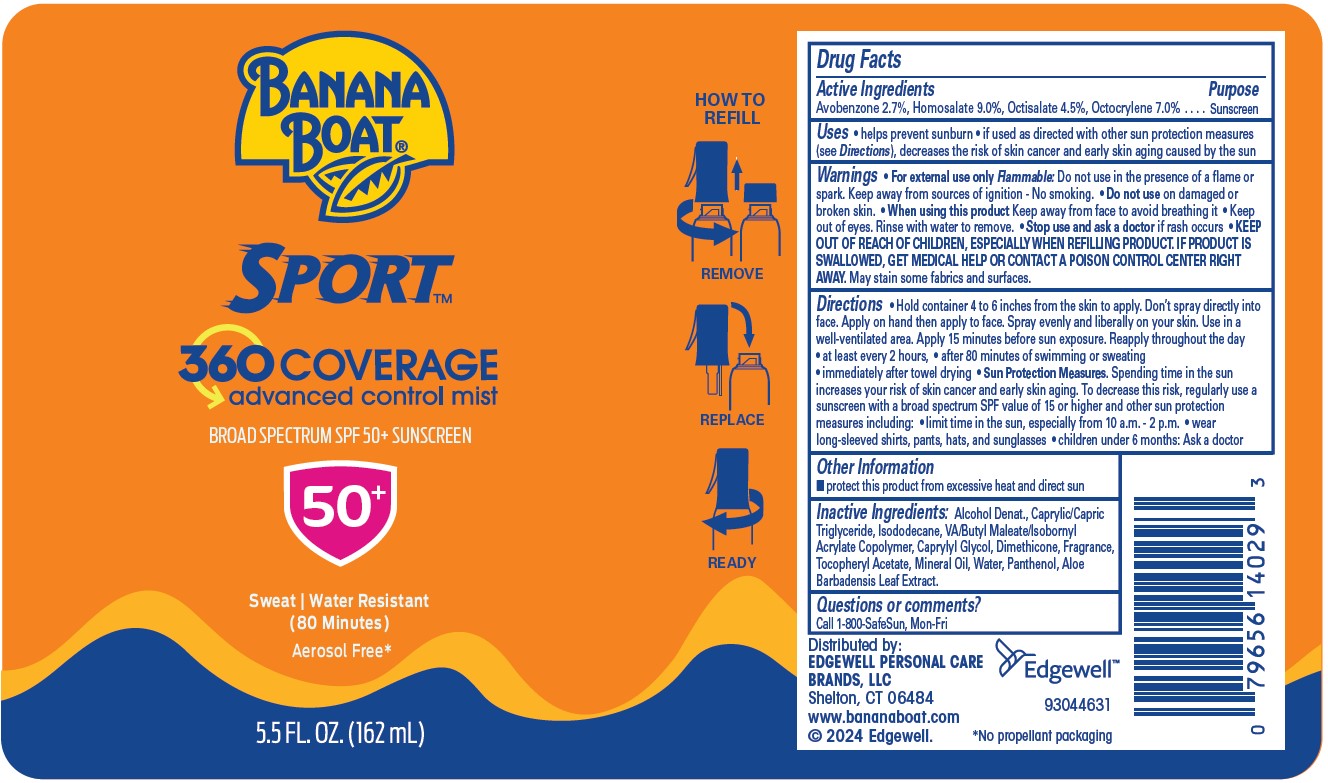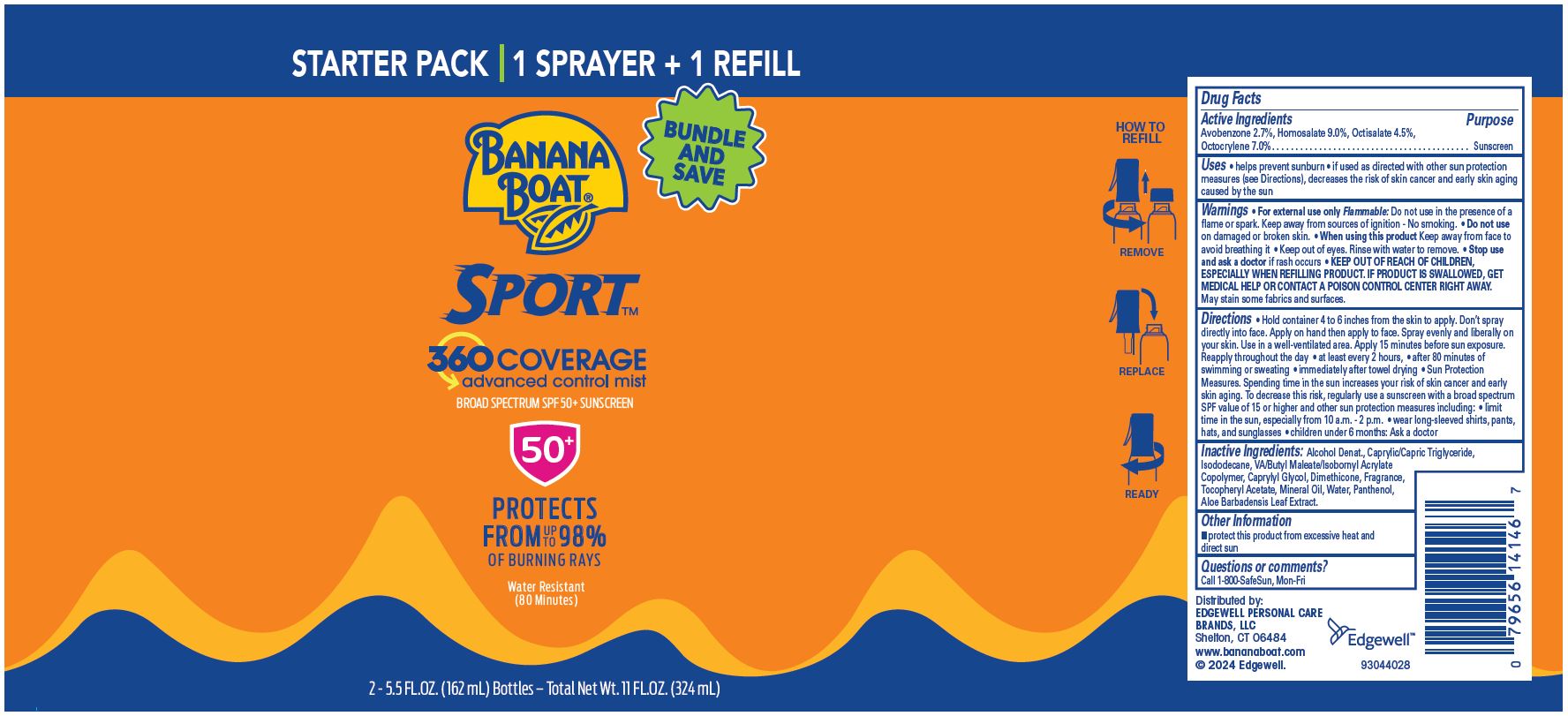 DRUG LABEL: BANANA BOAT
NDC: 63354-181 | Form: SPRAY
Manufacturer: Edgewell Personal Care Brands LLC
Category: otc | Type: HUMAN OTC DRUG LABEL
Date: 20251117

ACTIVE INGREDIENTS: HOMOSALATE 9 g/100 g; AVOBENZONE 2.7 g/100 g; OCTISALATE 4.5 g/100 g; OCTOCRYLENE 7 g/100 g
INACTIVE INGREDIENTS: MINERAL OIL; ALCOHOL; CAPRYLYL GLYCOL; MEDIUM-CHAIN TRIGLYCERIDES; ALPHA-TOCOPHEROL ACETATE; DIMETHICONE; WATER; ISODODECANE; ALOE VERA LEAF; PANTHENOL

Active Ingredients

Avobenzone 2.7%, Homosalate 9.0%, Octisalate 4.5%, Octocrylene 7.0%.

Purpose

Sunscreen

Uses

• helps prevent sunburn • if used as directed with other sun protection measures (see Directions), decreases the risk of skin cancer and early skin aging caused by the sun

Warnings

• For external use only, Flammable: Do not use in the presence of a flame or spark. Keep away from sources of ignition - No smoking.

May stain some fabrics and surfaces.

Do not use

on damaged or broken skin.

When using this product

Keep away from face to avoid breathing it • Keep out of eyes. Rinse with water to remove.

Stop use and ask a doctor

if rash occurs

KEEP OUT OF REACH OF CHILDREN,

ESPECIALLY WHEN REFILLING PRODUCT. IF PRODUCT IS SWALLOWED, GET MEDICAL HELP OR CONTACT A POISON CONTROL CENTER RIGHT AWAY.

Directions

• Hold container 4 to 6 inches from the skin to apply. Don’t spray directly into face. Apply on hand then apply to face. Spray evenly and liberally on your skin. Use in a well-ventilated area. Apply 15 minutes before sun exposure. Reapply throughout the day • at least every 2 hours, • after 80 minutes of swimming or sweating • immediately after towel drying • Sun Protection Measures. Spending time in the sun increases your risk of skin cancer and early skin aging. To decrease this risk, regularly use a sunscreen with a broad spectrum SPF value of 15 or higher and other sun protection measures including: • limit time in the sun, especially from 10 a.m. - 2 p.m. • wear long-sleeved shirts, pants, hats, and sunglasses • children under 6 months: Ask a doctor

Inactive Ingredients:

Alcohol Denat., Caprylic/Capric Triglyceride, Isododecane, VA/Butyl Maleate/Isobornyl Acrylate Copolymer, Caprylyl Glycol, Dimethicone, Fragrance, Tocopheryl Acetate, Mineral Oil, Water, Panthenol, Aloe Barbadensis Leaf Extract.

Other Information

- protect this product from excessive heat and direct sun

Questions or comments?

Call 1-800-SafeSun, Mon-Fri

Principal Display Panel

BANANA BOAT(R)
SPORT(TM)
360 COVERAGE
advanced control mist
BROAD SPECTRUM SPF 50+ SUNSCREEN
50+
Sweat | Water Resistant
(80 Minutes)
Aerosol Free*
5.5 FL. OZ. (162 mL)

AEROSOL-FREE REFILL AEROSOL-FREE
BANANA BOAT(R)
SPORT(TM)
360 COVERAGE
advanced control mist
BROAD SPECTRUM SPF 50+ SUNSCREEN
50+
Sweat | Water Resistant
(80 Minutes)
5.5 FL. OZ. (162 mL)

STARTER PACK 1 SPRAYER + 1 REFILL
BANANA BOAT(R)
BUNDLE AND SAVE
SPORT(TM)
360 COVERAGE
advanced control mist
BROAD SPECTRUM SPF 50+ SUNSCREEN
50+
PROTECTS
FROM UP TO 98%
OF BURNING RAYS
Water Resistant
(80 Minutes)
2 - 5.5 FL.OZ. (162 mL) Bottles – Total Net Wt. 11 FL.OZ. (324 mL)